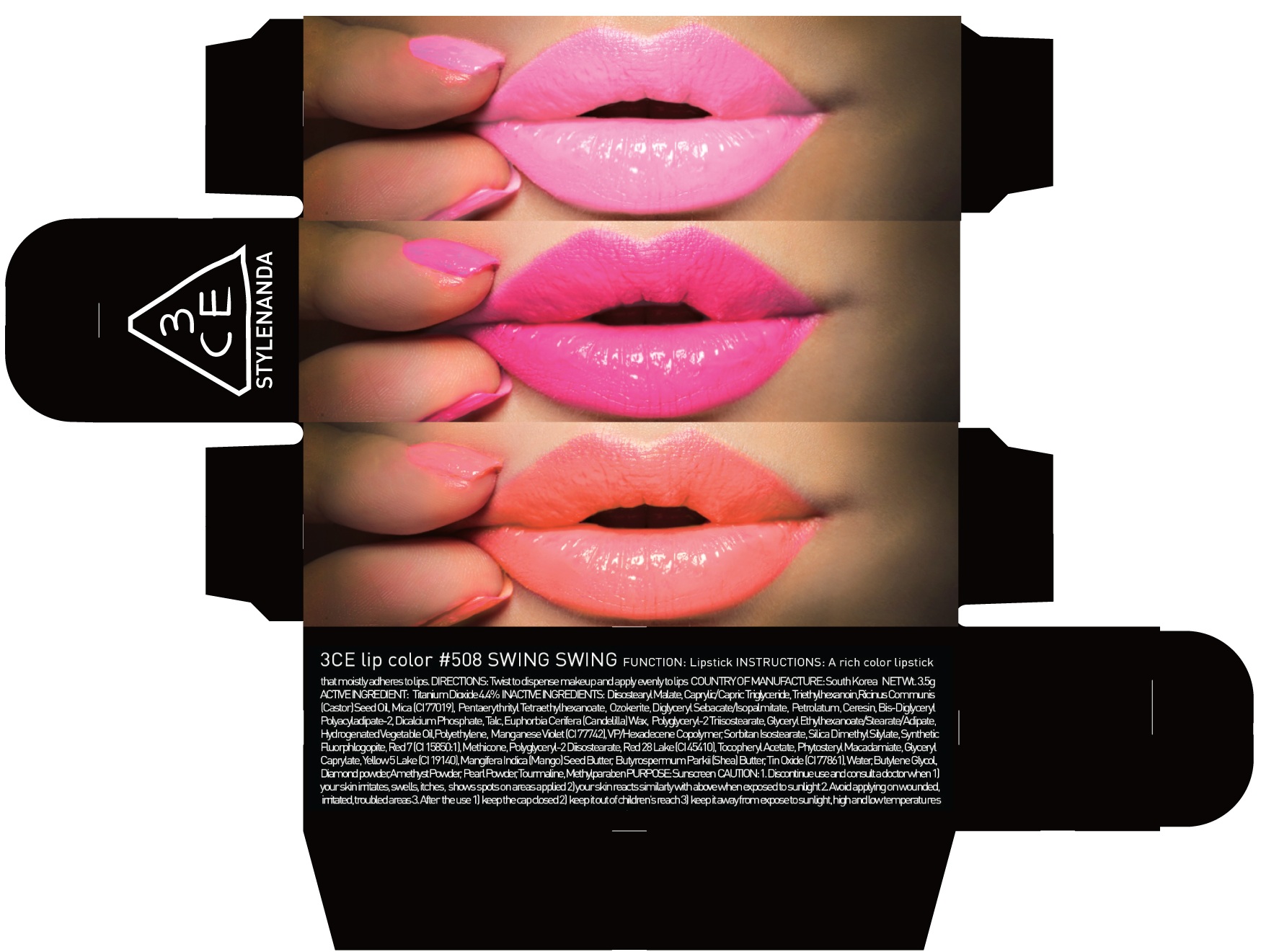 DRUG LABEL: 3CE LIP COLOR 508 SWING SWING
NDC: 60764-077 | Form: LIPSTICK
Manufacturer: Nanda Co., Ltd
Category: otc | Type: HUMAN OTC DRUG LABEL
Date: 20161007

ACTIVE INGREDIENTS: Titanium Dioxide 0.15 g/3.5 g
INACTIVE INGREDIENTS: Diisostearyl Malate; Triethylhexanoin

ACTIVE INGREDIENT

Active Ingredient: Titanium Dioxide 4.4%

INACTIVE INGREDIENT

Inactive Ingredients: Diisostearyl Malate, Caprylic/Capric Triglyceride, Triethylhexanoin, RicinusCommunis (Castor) Seed Oil, Mica (CI 77019), PentaerythritylTetraethylhexanoate, Ozokerite,DiglycerylSebacate/Isopalmitate, Petrolatum, Ceresin, Bis-Diglyceryl Polyacyladipate-2, Dicalcium Phosphate, Talc, Euphorbia Cerifera (Candelilla) Wax, Polyglyceryl-2 Triisostearate, Glyceryl Ethylhexanoate/Stearate/Adipate, Hydrogenated Vegetable Oil, Polyethylene, Manganese Violet (CI 77742), VP/Hexadecene Copolymer, SorbitanIsostearate, Silica Dimethyl Silylate, Synthetic Fluorphlogopite, Red 7 (CI 15850:1), Methicone, Polyglyceryl-2 Diisostearate, Red 28 Lake (CI 45410), Tocopheryl Acetate, PhytosterylMacadamiate, Glyceryl Caprylate, Yellow 5 Lake (CI 19140), MangiferaIndica (Mango) Seed Butter, ButyrospermumParkii (Shea) Butter, Tin Oxide (CI 77861), Water, Butylene Glycol, Diamond powder, Amethyst Powder, Pearl Powder, Tourmaline, Methylparaben

PURPOSE

Purpose: Sunscreen

CAUTION

CAUTION: 1. Discontinue use and consult a doctor when - your skin irritates, swells, itches, shows spots on areas applied - your skin reacts similarly with above when exposed to sunlight 2. Avoid applying on wounded, irritated, troubled areas 3. After the use - keep the cap closed - keep it out of children's reach - keep it away from expose to sunlight, high and low temperatures

DESCRIPTION

INSTRUCTIONS: A rich color lipstick that moistly adheres to lips.

Directions: Twist to dispense makeup and apply evenly to lips